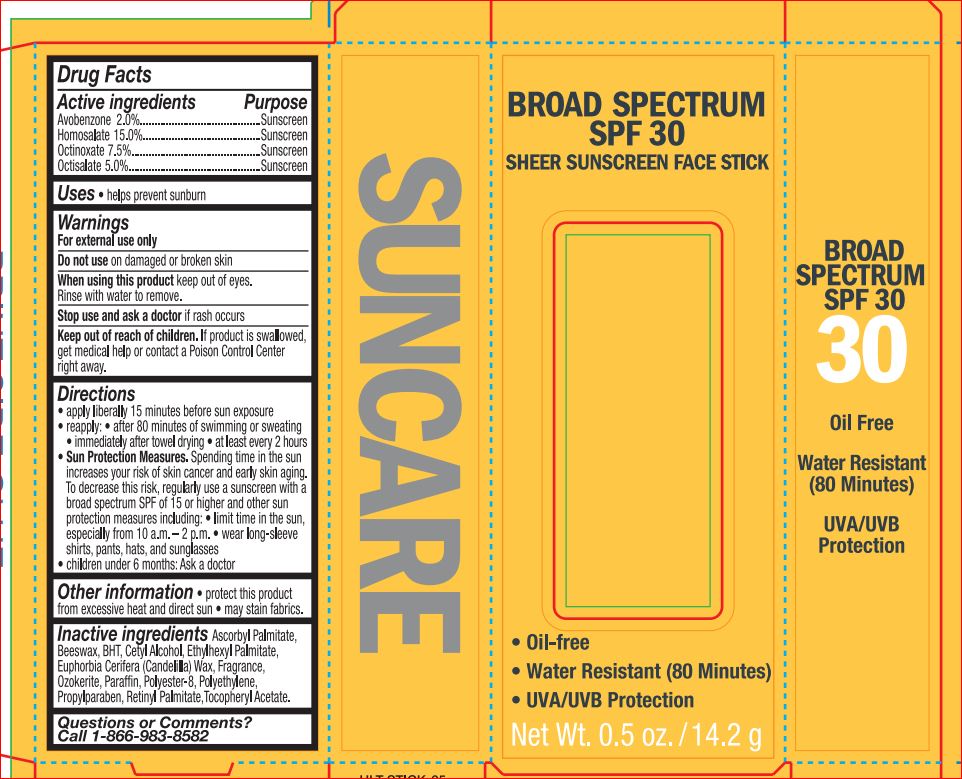 DRUG LABEL: SPF 30 Sheer sunscreen face
NDC: 62296-7778 | Form: STICK
Manufacturer: Ulta
Category: otc | Type: HUMAN OTC DRUG LABEL
Date: 20171010

ACTIVE INGREDIENTS: Avobenzone 2 g/100 g; Homosalate 15 g/100 g; Octinoxate 7.5 g/100 g; Octisalate 5 g/100 g
INACTIVE INGREDIENTS: Ascorbyl Palmitate; YELLOW WAX; BUTYLATED HYDROXYTOLUENE; Cetyl Alcohol; Ethylhexyl Palmitate; CANDELILLA WAX; CERESIN; PARAFFIN; POLYESTER-8 (1400 MW, CYANODIPHENYLPROPENOYL CAPPED); HIGH DENSITY POLYETHYLENE; Propylparaben; VITAMIN A PALMITATE; .ALPHA.-TOCOPHEROL ACETATE

Drug Facts

Active ingredients Purpose
Avobenzone 2.00%........................................................................Sunscreen
Octisalate 3.00%............................................................................Sunscreen
Octocrylene 7.00%.........................................................................Sunscreen
Oxybenzone 3.00%........................................................................Sunscreen

INDICATIONS AND USAGE

Uses • helps prevent sunburn

Warnings
For external use only
Flammable: Do not use near heat, flame, or while smoking.
Do not use on damaged or broken skin
When using this product • Keep out of eyes. Rinse eyes with water to remove.
• Keep away from face to avoid breathing it • Do not puncture or incinerate.
Contents under pressure. Do not store at temperatures above 120ºF.
Stop use and ask a doctor if rash occurs

Keep out of reach of children. If product is swallowed, get medical help or contact a Poison Control Center right away.

Directions
• apply liberally 15 minutes before sun exposure
• reapply:
• after 80 minutes of swimming or sweating
• immediately after towel drying
• at least every 2 hours
• Sun Protection Measures. Spending time in the sun increases your risk
of skin cancer and early skin aging. To decrease this risk, regularly use
a sunscreen with a broad spectrum SPF of 15 or higher and other
sun protection measures including:
• limit time in the sun, especially from 10 a.m. – 2 p.m.
• wear long-sleeve shirts, pants, hats, and sunglasses
• children under 6 months: Ask a doctor

Inactive ingredients

Ascorbyl Palmitate
Beeswax
BHT
Cetyl Alcohol
Ethylhexyl Palmitate
Euphorbia Cerifera (Candelilla) Wax
Fragrance
Ozokerite
Paraffin
Polyester-8
Polyethylene
Propylparaben
Retinyl Palmitate
Tocopheryl Acetate